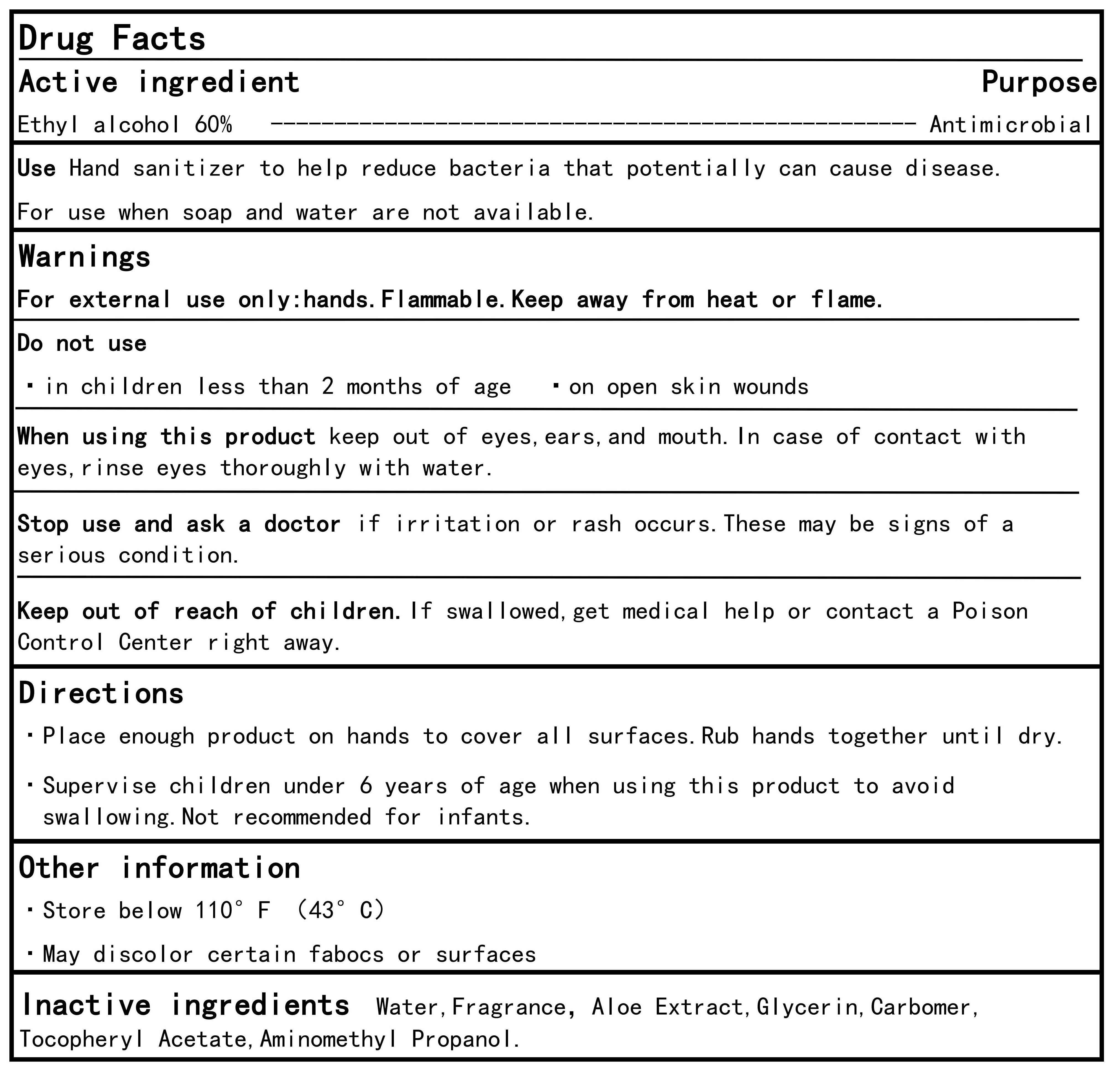 DRUG LABEL: ELLEN HAND SANITIZER2
NDC: 85537-102 | Form: SPRAY
Manufacturer: PT. SUPER HOME PRODUCT INDONESIA
Category: otc | Type: HUMAN OTC DRUG LABEL
Date: 20250421

ACTIVE INGREDIENTS: ALCOHOL 60 mL/100 mL
INACTIVE INGREDIENTS: .ALPHA.-TOCOPHEROL ACETATE 0.001 mL/100 mL; AMINOMETHYLPROPANOL 0.005 mL/100 mL; GLYCERIN 2 mL/100 mL; CARBOMER 0.01 mL/100 mL; AQUA 36.884 mL/100 mL; ALOE 0.1 mL/100 mL; FRAGRANCE LAVENDER & CHIA F-153480 1 mL/100 mL

USE

Use Hand sanitizer to help reduce bacteria that potentially can cause diseaseFor use when soap and water are not ava'lable.

Warnings

For external use only:hands.Flammable.Keep away from heat or flame

Inactive ingredients

Water,Fragrance, Aloe Extract,Glycerin, CarbomerTocopherylAcetate,Aminomethyl Propanol.

Directions

- Place enough product on hands to cover all surfaces.Rub hands together until dry.
- Supervise children under 6 years of age when using this product to avoidswalowing.Not recommended for infants.

Keep out of reach of children.

lf swallowed, get medical help or contact a PoisonControlCenter right away.

Purpose

Antimicrobial，Hand Sanitizer

Active ingredient

Ethyl alcohol 60%v/v Purpose：Antimicrobial